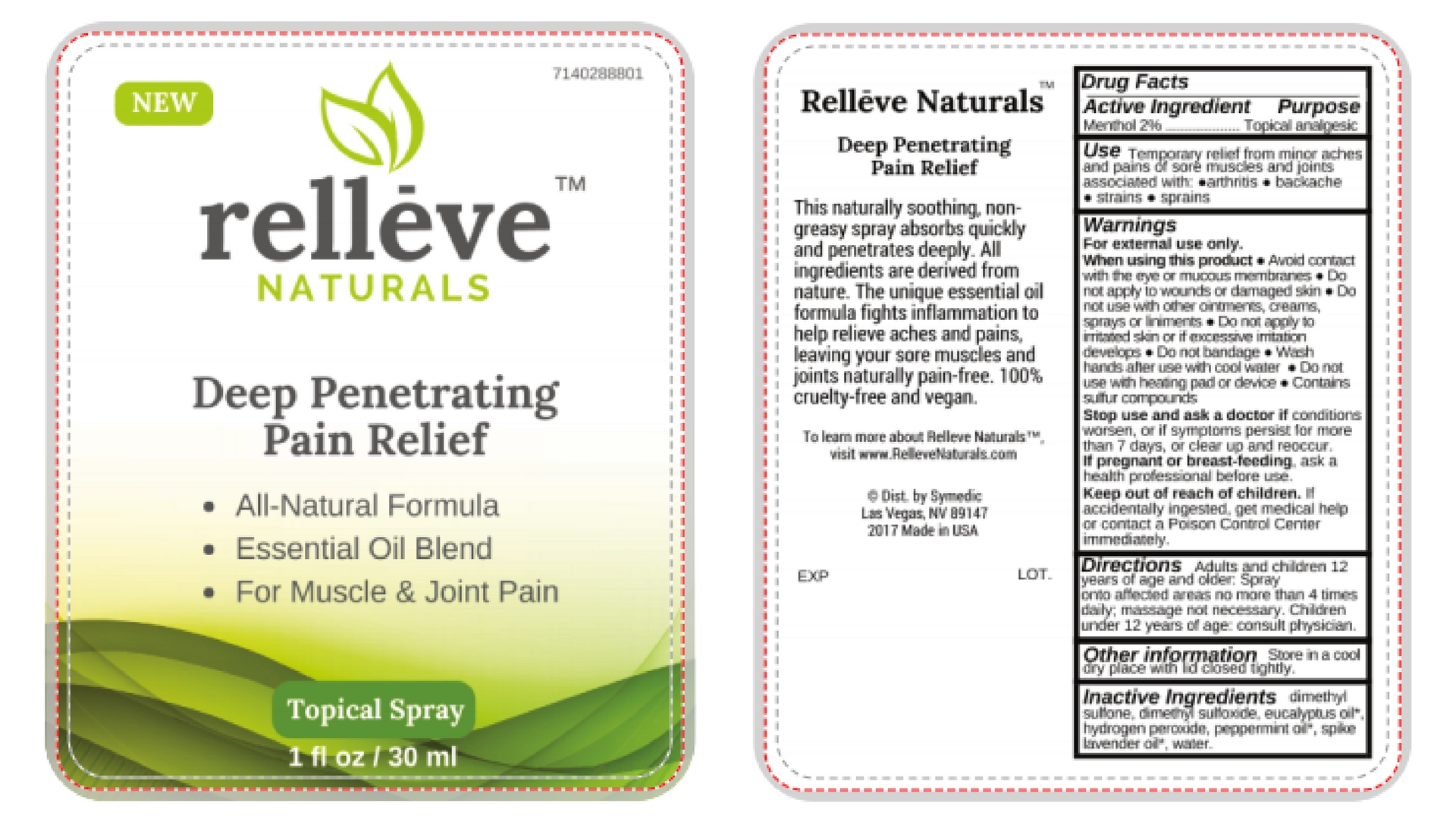 DRUG LABEL: The Relief Company
NDC: 71402-101 | Form: GEL
Manufacturer: Symedic LLC
Category: otc | Type: HUMAN OTC DRUG LABEL
Date: 20190903

ACTIVE INGREDIENTS: MENTHOL 4 g/100 mL
INACTIVE INGREDIENTS: CARBOMER HOMOPOLYMER, UNSPECIFIED TYPE; TROLAMINE; MELALEUCA ALTERNIFOLIA LEAF; ALOE VERA LEAF; PHENOXYETHANOL; ALPHA-TOCOPHEROL ACETATE; CANNABIS SATIVA SEED OIL; WATER; ARNICA MONTANA; ISOPROPYL ALCOHOL; CAMPHOR (NATURAL); ILEX PARAGUARIENSIS LEAF; ETHYLHEXYLGLYCERIN

Active Ingredient

Menthol 2%

Purpose

Topical analgesic

Use

Temporary relief from minor aches and pains of sore muscles & joints associated with

- arthritis
- simple backache
- strains
- bruises
- sprains.

Warnings

For external use only.

When using this product

- Avoid contact with the eye or mucous membranes
- Do not apply to wounds or damaged skin
- Do not use with other ointments, creams, sprays or liniments
- Do not apply to irritated skin or if excessive irritation develops
- Do not bandage
- Wash hands after use with cool water
- Do not use with heating pad or device
- Contains sulfur compounds.

Stop use and ask a doctor if conditions worsen, or if symptoms persist for more than 7 days, or clear up and reoccur.

PREGNANCY OR BREAST FEEDING

If pregnant or breast-feeding, ask a health professional before use.

Keep out of reach of children. If accidentally ingested, get medical help or contact a Poison Control Center immediately.

Directions

Adults and children 12 years of age and older: Spray onto affected areas no more than 4 times daily; massage not necessary. Children under 12 years of age: consult a physician.

Other Information

Store in a cool dry place with lid closed tightly.

Inactive Ingredients

dimethyl sulfone, dimethyl sulfoxide, eucalyptus oil*, hydrogen peroxide, peppermint oil*, spike lavender oil*, water.

Relleve Naturals - Menthol Spray [7140288801]

New

7140288801

Relleve Naturals

Deep Penetrating Pain Relief

- All-Natural Formula
- Essential Oil Blend
- For Muscle & Joint Pain

Topical Spray

1 fl oz / 30 ml